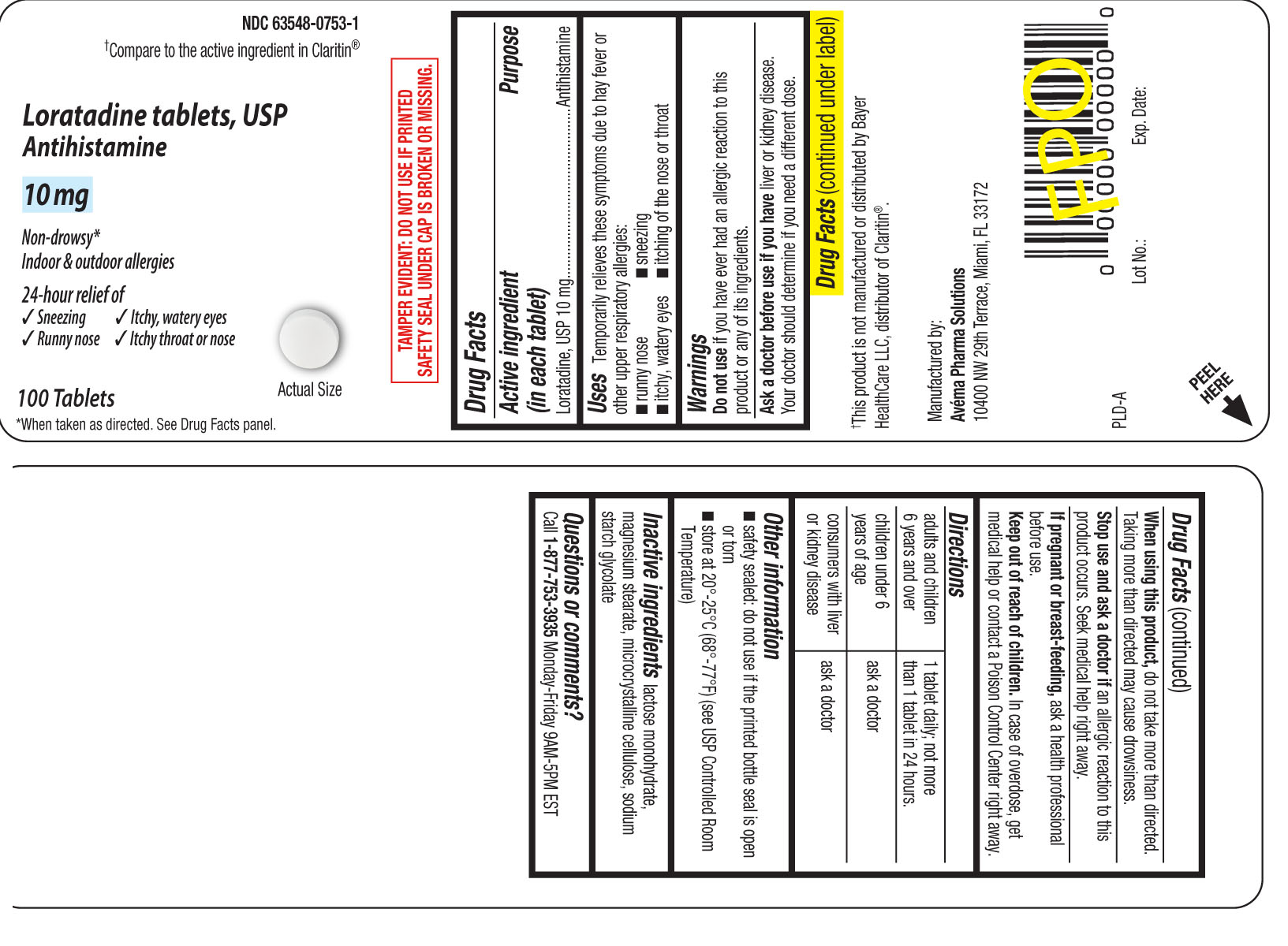 DRUG LABEL: Loratadine
NDC: 63548-0753 | Form: TABLET
Manufacturer: PLD Acquisitions LLC DBA Avéma Pharma Solutions
Category: otc | Type: HUMAN OTC DRUG LABEL
Date: 20230504

ACTIVE INGREDIENTS: LORATADINE 10 mg/1 1
INACTIVE INGREDIENTS: LACTOSE MONOHYDRATE; MAGNESIUM STEARATE; MICROCRYSTALLINE CELLULOSE; SODIUM STARCH GLYCOLATE TYPE A POTATO

Drug Facts

Active ingredient (in each tablet)

Loratadine, USP 10 mg

Purpose

Antihistamine

Uses

Temporarily relieves these symptoms due to hay fever or other upper respiratory allergies:

- runny nose
- sneezing
- itchy, watery eyes
- itching of the nose or throat

Warnings

Do not use

if you have ever had an allergic reaction to this product or any of its ingredients.

Ask a doctor before use if you have

liver or kidney disease. Your doctor should determine if you need a different dose.

When using this product,

do not take more than directed. Taking more than directed may cause drowsiness.

Stop use and ask a doctor if

an allergic reaction to this product occurs. Seek medical help right away

If pregnant or breast-feeding,

ask a health professional before use.

Keep out of reach of children.

In case of overdose, get medical help or contact a Poison Control Center right away.

Directions

adults and children 6 years and over | 1 tablet daily;not more than 1 tablet in 24 hours
children under 6 years of age | ask a doctor
consumers with liver or kidney disease | ask a doctor

Other information

- safety sealed: do not use if the printed bottle seal is open or torn
- store at 20º-25ºC (68º-77ºF) (see USP Controlled Room Temperature)

Inactive ingredients

lactose monohydrate,magnesium stearate, microcrystalline cellulose, sodium starch glycolate

Questions or comments?

Call 1-877-753-3935 Monday-Friday 9 AM-5 PM EST

Principal Display Panel

†Compare to the active ingredient in Claritin®

Loratadine tablets, USP

Antihistamine

10 mg

Non-drowsy*

Indoor & outdoor allergies

24-hour relief of

- sneezing
- itchy, watery eyes
- runny nose
- itchy throat or nose

100 Tablets

*When taken as directed. See Drug Facts panel

TAMPER EVIDENT: DO NOT USE IF PRINTED SAFETY SEAL UNDER CAP IS BROKEN OR MISSING

†This product is not manufactured or distributed by Bayer HealthCare LLC, distributor of Claritin®

Manufactured by:

Avema Pharm Solutions

10400 NW 29th Terrace, Miami, FL 33172

Package Label

Loratadine 10 mg Tablets